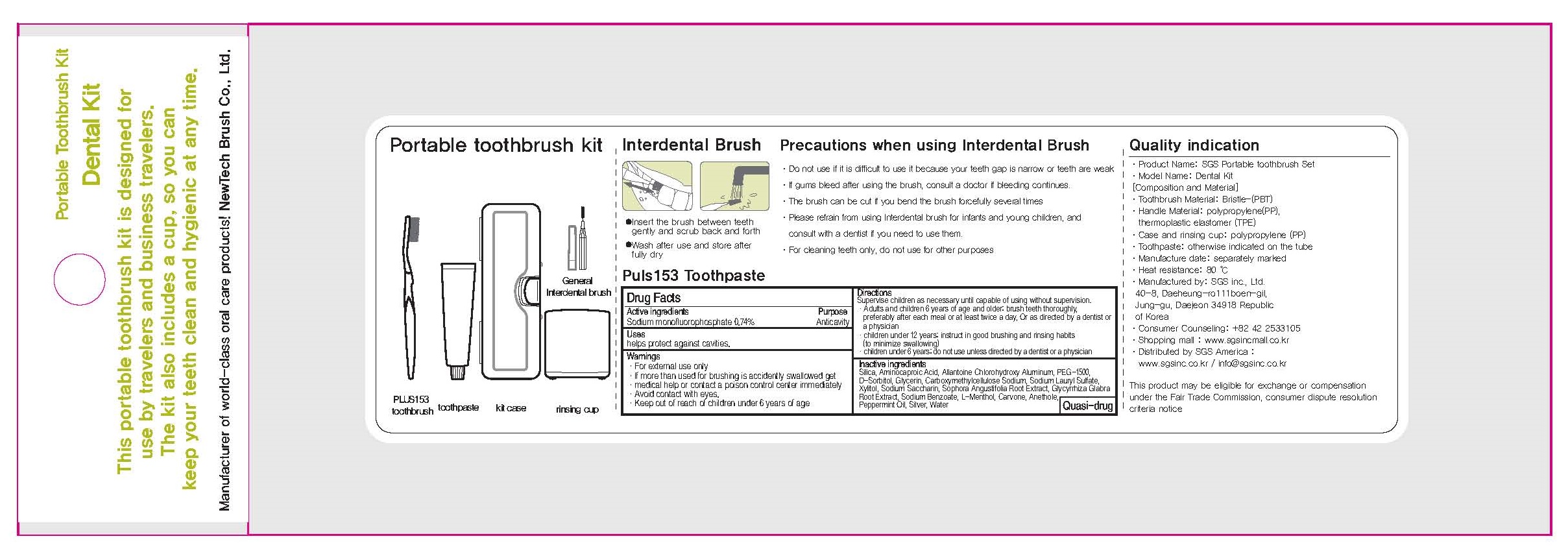 DRUG LABEL: PLUS153 Toothpast e
NDC: 71553-010 | Form: PASTE, DENTIFRICE
Manufacturer: SGS Inc.
Category: otc | Type: HUMAN OTC DRUG LABEL
Date: 20170707

ACTIVE INGREDIENTS: Sodium monofluorophosphate 0.29 g/40 g
INACTIVE INGREDIENTS: Aminocaproic Acid; Glycerin

ACTIVE INGREDIENT

Active ingredients: Sodium monofluorophosphate 0.74%

INACTIVE INGREDIENT

Inactive ingredients: Silica, Aminocaproic Acid, Allantoine Chlorohydroxy Aluminum, PEG-1500, D-Sorbitol, Glycerin, Carboxymethylcellulose Sodium, Sodium Lauryl Sulfate, Xylitol, Sodium Saccharin, Sophora Angustifolia Root Extract, Glycyrrhiza Glabra Root Extract, Sodium Benzoate, L-Menthol, Carvone, Anethole, Peppermint Oil, Silver, Water

PURPOSE

Purpose: Anticavity

WARNINGS

Warnings: For external use only If more than used for brushing is accidently swallowed get medical help or contact a poison control center immediately Avoid contact with eyes.

Keep out of reach of children under 6 years of age.

Uses

Uses: Helps protect against cavities.

Directions

Supervise children as necessary until capable of using without supervision.

- Adults and children 6 years of age and older: brush teeth thoroughly, preferably after each meal or at least twice a day, Or as directed by a dentist or a physician

- children under 12 years: instruct in good brushing and rinsing habits (to minimize swallowing)

- children under 6 years: do not use unless directed by a dentist or a physician